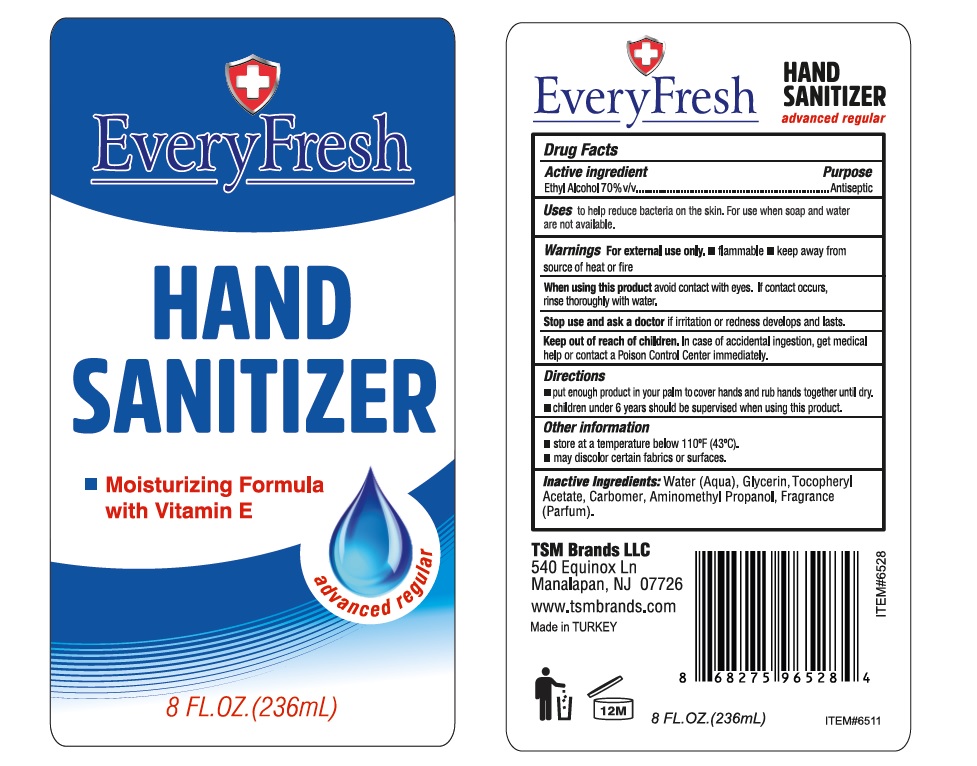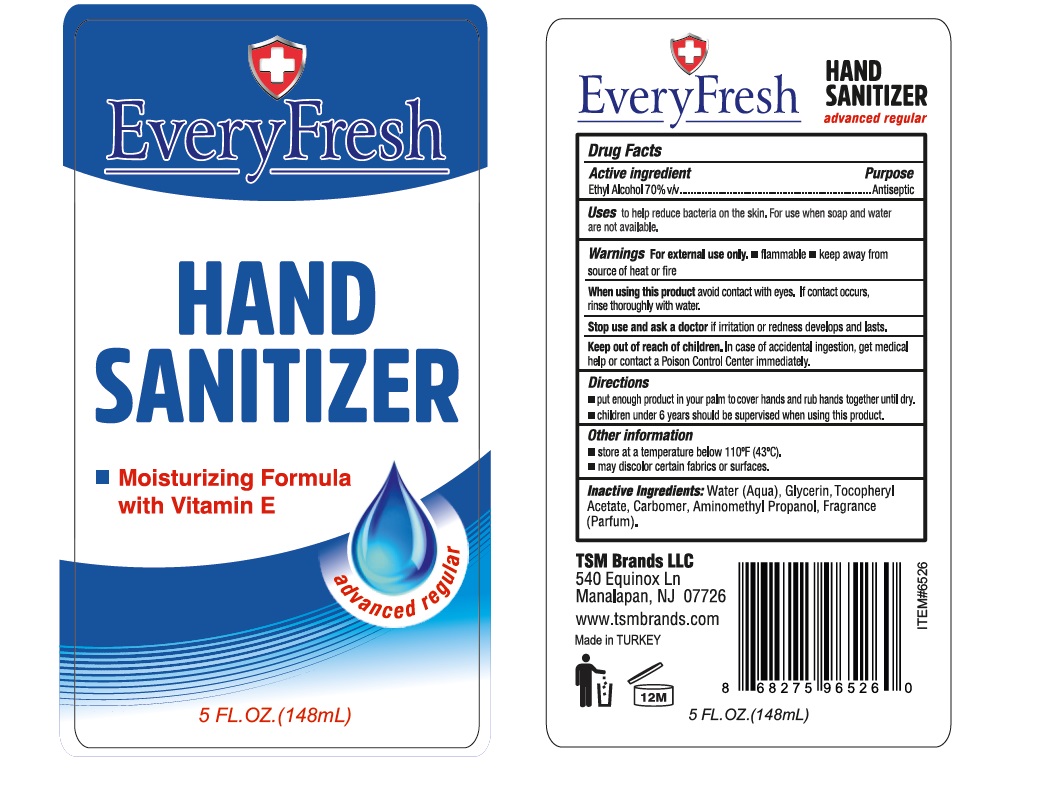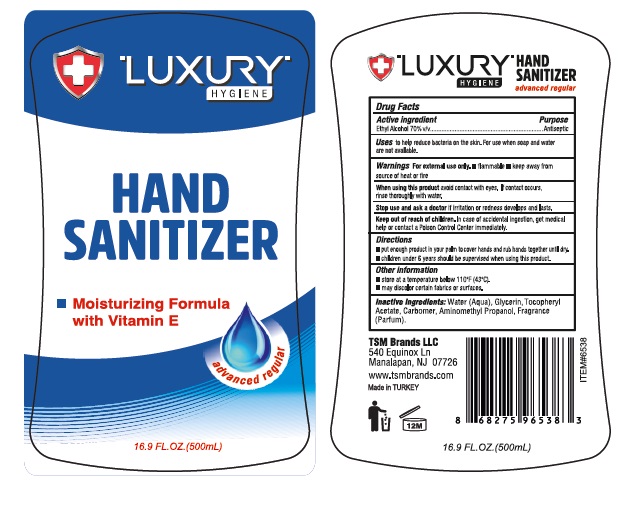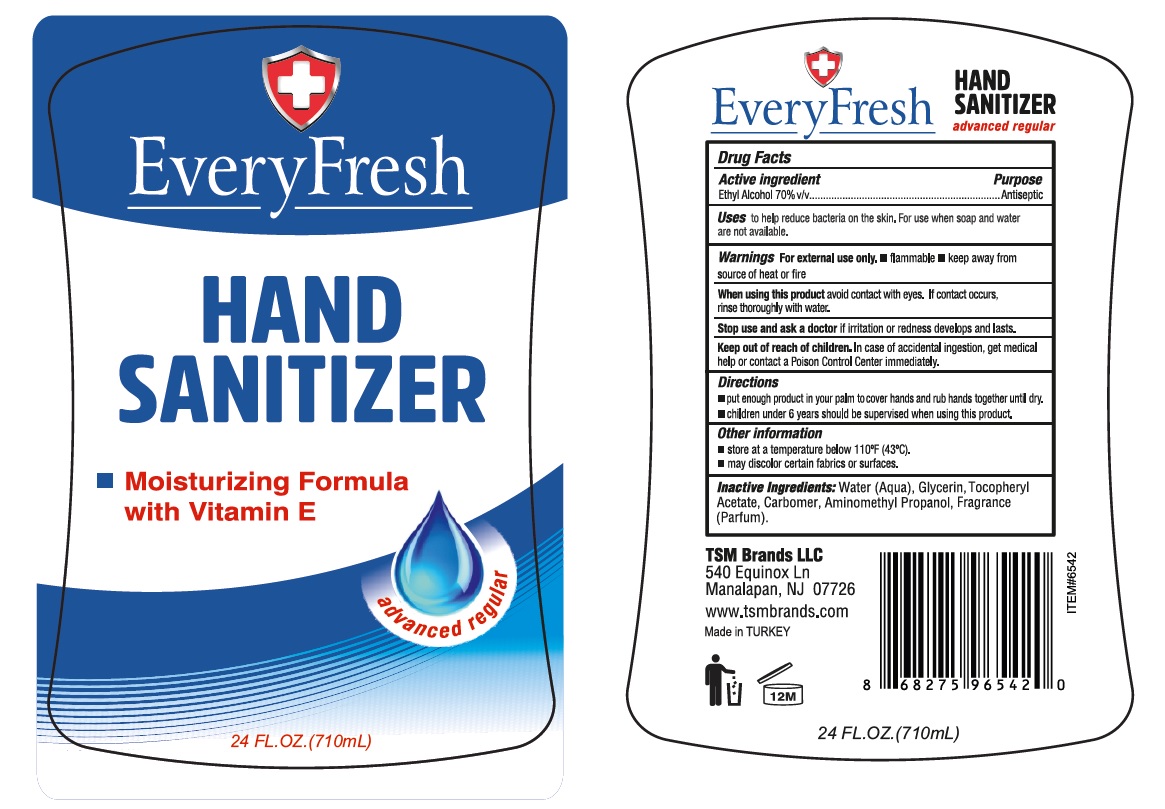 DRUG LABEL: Every Fresh Hand Sanitizer
NDC: 76772-015 | Form: GEL
Manufacturer: TSM ITHALAT IHRACAT SANAYI VE DIS TICARET LIMITED SIRKETI
Category: otc | Type: HUMAN OTC DRUG LABEL
Date: 20210121

ACTIVE INGREDIENTS: ALCOHOL 70 mL/100 mL
INACTIVE INGREDIENTS: WATER; CARBOMER INTERPOLYMER TYPE A (ALLYL SUCROSE CROSSLINKED); GLYCERIN; AMINOMETHYLPROPANOL; .ALPHA.-TOCOPHEROL ACETATE

Every Fresh Hand sanitizer

Drug Facts

Active Ingredient

Ethyl Alcohol, 70% v/v

Purpose

Antiseptic

Uses

- To help reduce bacteria on the skin
- For use when soap and water are not available

Warnings

For external use only. Flammable, keep away from fire or flame.

When using this product keep out of eyes. If contact with eyes occurs, rinse promptly and thoroughly with water.

Stop use and ask a doctor if significant irritation or sensitization develops.

Keep out of reach of children. If swallowed, get medical help or contact a Poison Control Center right away.

Directions

-Put enough product on your palm to cover hands and rub your hands together until dry.

-Children under 6years should be supervised when using this product.

Other Information

Store below 43°C (110°F)

May discolor certain fabrics

Inactive Ingredients

carbomer, aminomethyl propanol, glycerin, water, tocopheryl acetate (Vit E).